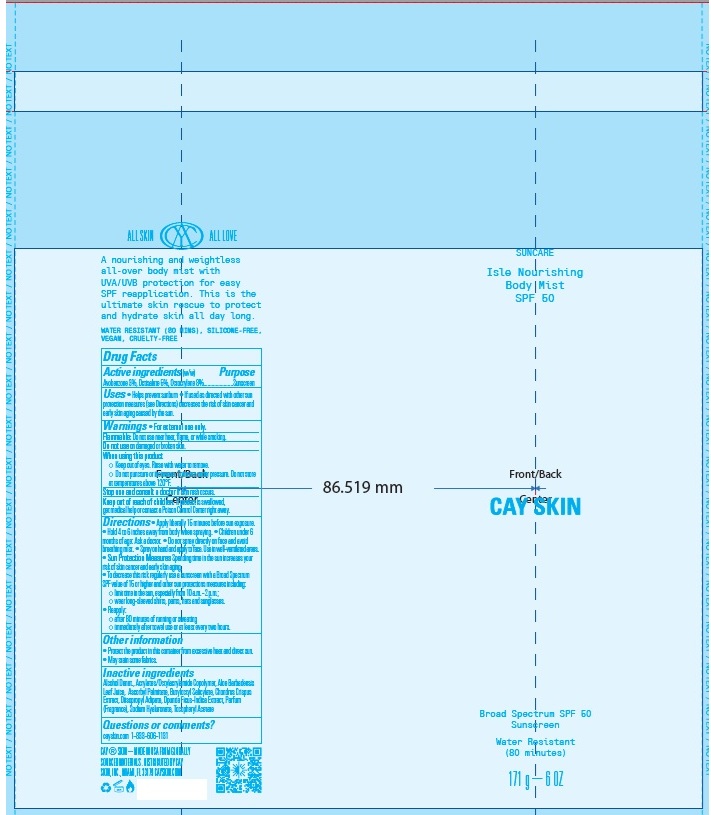 DRUG LABEL: Cay Skin Isle Nourishing Body Mist SPF 50
NDC: 82657-009 | Form: AEROSOL, SPRAY
Manufacturer: Cay Skin, Inc.
Category: otc | Type: HUMAN OTC DRUG LABEL
Date: 20250116

ACTIVE INGREDIENTS: AVOBENZONE 30 mg/1 g; OCTISALATE 50 mg/1 g; OCTOCRYLENE 80 mg/1 g
INACTIVE INGREDIENTS: SODIUM HYALURONATE; ACRYLATES/OCTYLACRYLAMIDE COPOLYMER (40000 MW); ALPHA-TOCOPHEROL ACETATE; ALOE VERA LEAF; DIISOPROPYL ADIPATE; ALCOHOL; ASCORBYL PALMITATE; OPUNTIA FICUS-INDICA; CHONDRUS CRISPUS; BUTYLOCTYL SALICYLATE

Cay Skin Isle Nourishing Body Mist SPF 50

Active ingredients

Avobenzone 3%

Octisalate 5%

Octocrylene 8%

Purpose

Sunscreen

Uses

- Helps prevent sunburn
- If used as directed with other sun protection measures (see Directions) decreases the risk of skin cancer and early skin aging caused by the sun.

Warnings

For external use only.

Do not use

on damaged or broken skin.

When using this product

- Keep out of eyes. Rinse with water to remove.
- Do not puncture or incinerate. Contents under pressure. Do not store at temperatures above 120F.

Stop use and consult a doctor

if skin rash occurs.

Keep out of reach of children.

If product is swallowed, get medical help or contact a Poison Control Center right away.

Directions

- Apply liberally 15 minutes before sun exposure.
- Hold 4 to 6 inches away from body when spraying.
- Children under 6 months of age: Ask a doctor.
- Do not spray directly on face and avoid breathing mist.
- Spray on hand and apply to face. Use in well-ventilated areas.
- Sun Protection Measures Spending time in the sun increases your risk of skin cancer and early skin aging.
- To decrease this risk regularly use a sunscreen with a Broad Spectrum SPF value of 15 or higher and other sun protections measures including:
- limit time in the sun, especially from 10 a.m. - 2 p.m.
- wear long-sleeved shirts, pants, hats and sunglasses.
- Reapply:
- after 80 minutes of running or sweating
- immediately after towel use or at least every two hours.

Other information

- Protect the product in this container from excessive heat and direct sun.
- May stain some fabrics.

Inactive ingredients

Alcohol Denat., Acrylates/Octylacrylamide Copolymer, Aloe Barbadensis Leaf Juice, Ascorbyl Palmitate, Butyloctyl Salicylate, Chondrus Crispus Extract, Diisopropyl Adipate, Opuntia Ficus-Indica Extract, Parfum (Fragrance), Sodium Hyaluronate, Tocopheryl Acetate

Questions or comments?

cayskin.com 1-833-606-1131

Company Information

DISTRIBUTED BY CAY SKIN, INC.,

MIAMI, FL 33179 CAYSKIN.COM